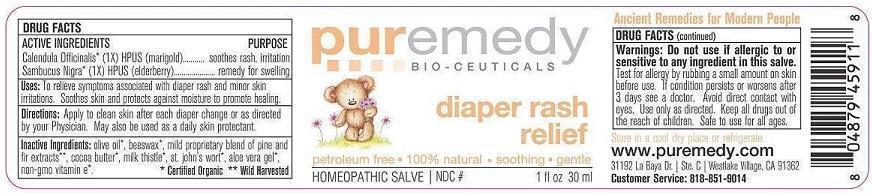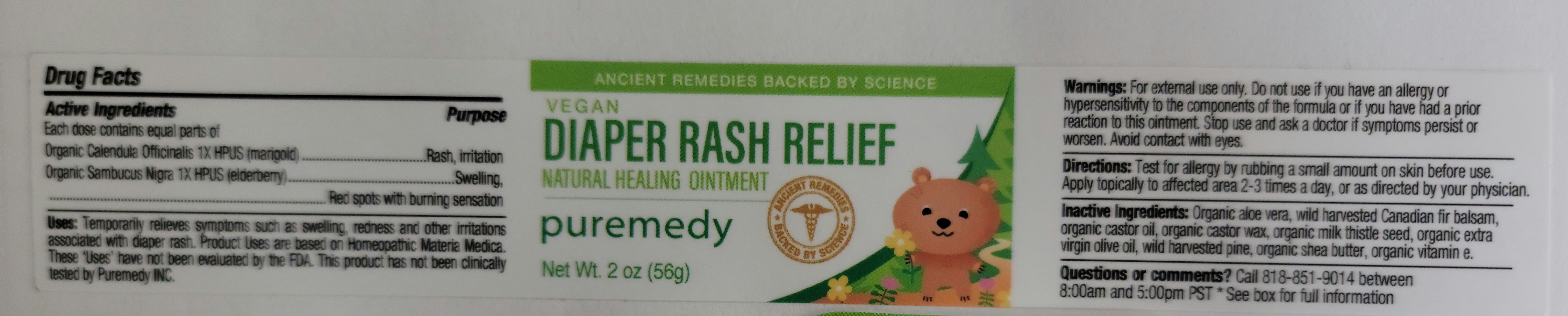 DRUG LABEL: BABY DIAPER RASH
NDC: 52810-216 | Form: SALVE
Manufacturer: PUREMEDY
Category: homeopathic | Type: HUMAN OTC DRUG LABEL
Date: 20240111

ACTIVE INGREDIENTS: CALENDULA OFFICINALIS FLOWER 1 [hp_X]/100 mL; SAMBUCUS NIGRA FLOWER 1 [hp_X]/100 mL
INACTIVE INGREDIENTS: OLIVE OIL; YELLOW WAX; CANADA BALSAM; COCOA BUTTER; SILYBUM MARIANUM SEED; ST. JOHN'S WORT; ALOE VERA LEAF; .ALPHA.-TOCOPHEROL

DIAPER RASH RELIEF (52810-216)

ACTIVE INGREDIENTS

ORG. CALENDULA OFFICINALIS (1X) HPUS) (MARIGOLD)

ORG. SAMBUCUS NIGRA (1X) HPUS (ELDERBERRY)

PURPOSE

SOOTHES RASH, IRRITATION

REMEDY FOR SWELLING

INDICATIONS AND USAGE

USES: TO RELIEVE SYMPTOMS ASSOCIATED WITH DIAPER RASH AND MINOR SKIN IRRITATIONS. SOOTHES SKINS AND PROTECTS AGAINST MOISTURE TP PROMOTE HEALING.

DOSAGE AND ADMINISTRATION

DIRECTIONS: APPLY TO CLEAN SKIN AFTER EACH DIAPER CHANGE OR AS DIRECTED BY YOUR PHYSICIAN. MAY ALSO BE USED AS A DAILY SKIN PROTECTANT.

INACTIVE INGREDIENT

INACTIVE INGREDIENTS: ORG. OLIVE OIL, ORG. BEESWAX, MILD PROPRIETARY BLEND OF PINE AND FIR EXTRACTS, ORG. COCOA BUTTER, ORG. MILK THISTLE, ORG. ST. JOHN'S WORT, ORG. ALOE VERA GEL, ORG. NON-GMO VITAMIN E

WARNINGS

WARNINGS: DO NOT USE IF ALLERGIC TO OR SENSITIVE TO ANY INGREDIENT IN THIS SALVE. TEST FOR ALLERGY BY RUBBING A SMALL AMOUNT ON SKIN BEFORE USE. IF CONDITION PERSISTS OR WORSENS AFTER 3 DAYS SEE A DOCTOR. AVOID DIRECT CONTACT WITH EYES. USE ONLY AS DIRECTED. KEEP ALL DRUGS OUT OF USE OF CHILDREN. SAFE TO USE FOR ALL AGES.

KEEP ALL DRUGS OUT OF REACH OF CHILDREN.

STORAGE AND HANDLING

STORE IN A COOL DRY PLACE OR REFRIGERATE.

QUESTIONS

CUSTOMER SERVICE 818-851-9014